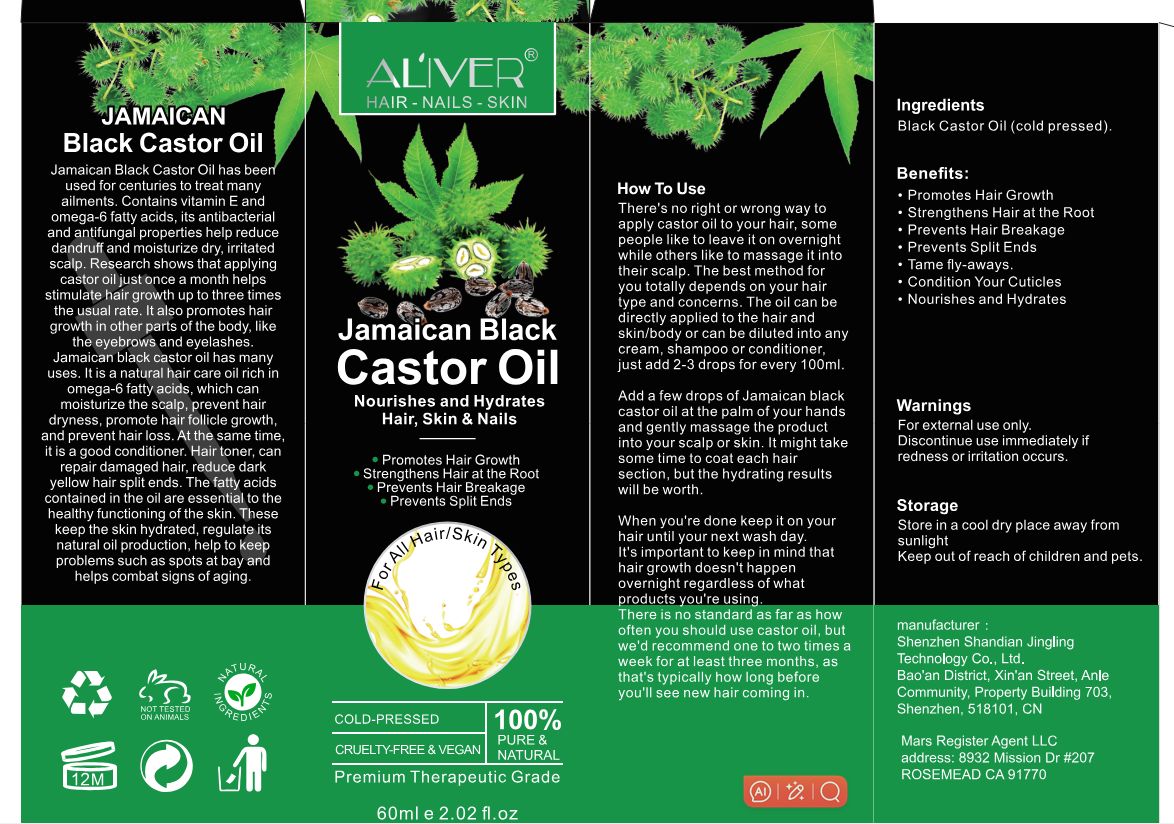 DRUG LABEL: ALIVER Jamaican Black Castor Oil
NDC: 83804-111 | Form: OIL
Manufacturer: Shenzhen Shandian Jingling Technology Co., Ltd.
Category: otc | Type: HUMAN OTC DRUG LABEL
Date: 20240524

ACTIVE INGREDIENTS: CASTOR OIL 100 g/100 mL

83804-111-01

Active Ingredient

black Castor oil（cold pressed） 100%

Purpose

Promotes Hair Growth
Strengthens Hair at the Root
Prevents Hair Breakage
Prevents Split ends

Use

Add a few drops of Jamaican black castor oil at the palm of your hands and gently massage the productinto your scalp or skin.lt might takesome time to coat each hairsection, but the hydrating result swill be worth

Warnings

For external use only.Discontinue use immediately if redness or irritation occurs

Do not use

Discontinue use immediately if redness or irritation occurs

When Using

There's no right or wrong way to apply castor oil to your hair, some people like to leave it on overnight while others like to massage it into their scalp. The best method for you totally depends on your hair type and concerns. The oil can be directly applied to the hair and skin/body or can be diluted into any cream, shampoo or conditioner, just add 2-3 drops for every 100ml.

Add a few drops of Jamaican black castor oil at the palm of your hands and gently massage the product into your scalp or skin. It might take some time to coat each hair section, but the hydrating results will be worth.
When you're done keep it on your hair until your next wash day.
It's important to keep in mind that hair growth doesn't happen overnight regardless of what products you're using.
There is no standard as far as how often you should use castor oil, but we'd recommend one to two times a week for at least three months, as that's typically how long before you'll see new hair coming in.

Stop Use

Discontinue use immediately if redness or irritation occurs

Keep Oot Of Reach Of Children

Store in a cool dry place away from sunlight
Keep out of reach of children and pets.

Directions

There's no right or wrong way to apply castor oil to your hair, someoeople like to leave it on overnighwhile others like to massage it intotheir scalp.The best method for you totally depends on your hairtype and concerns.The oil can bedirectlvaopledto the hair angskin/body or can be diluted into anycream,shampoo or conditioner，just add 2-3 drops for every 100ml

Inactive ingredients

None